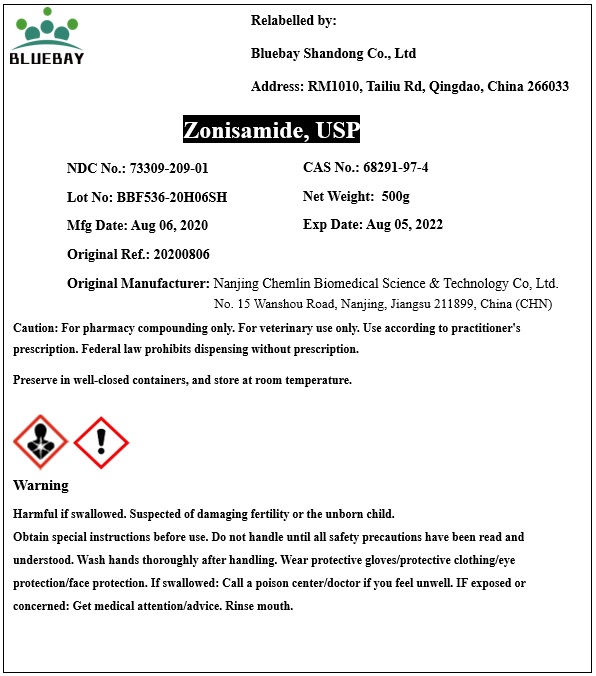 DRUG LABEL: Zonisamide
NDC: 73309-209 | Form: POWDER
Manufacturer: BLUEBAY SHANDONG CO.,LTD
Category: other | Type: BULK INGREDIENT
Date: 20201111

ACTIVE INGREDIENTS: ZONISAMIDE 1 g/1 g

Zonisamide